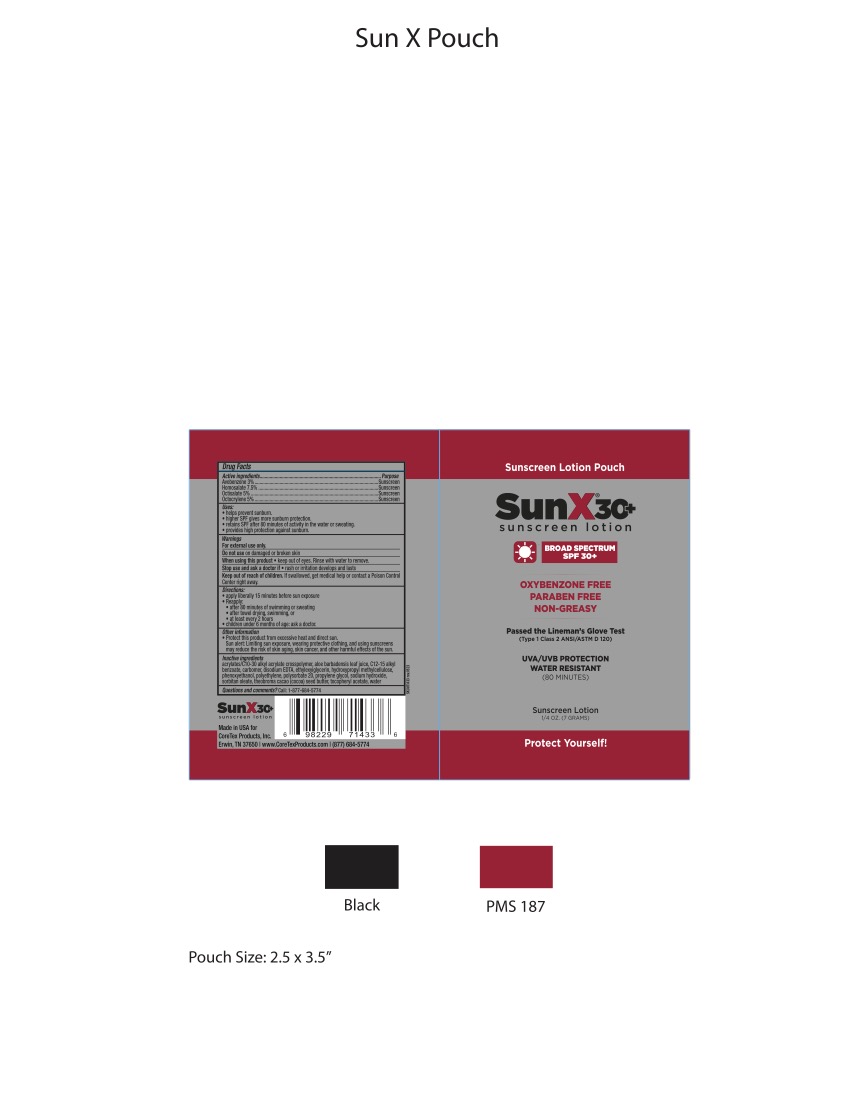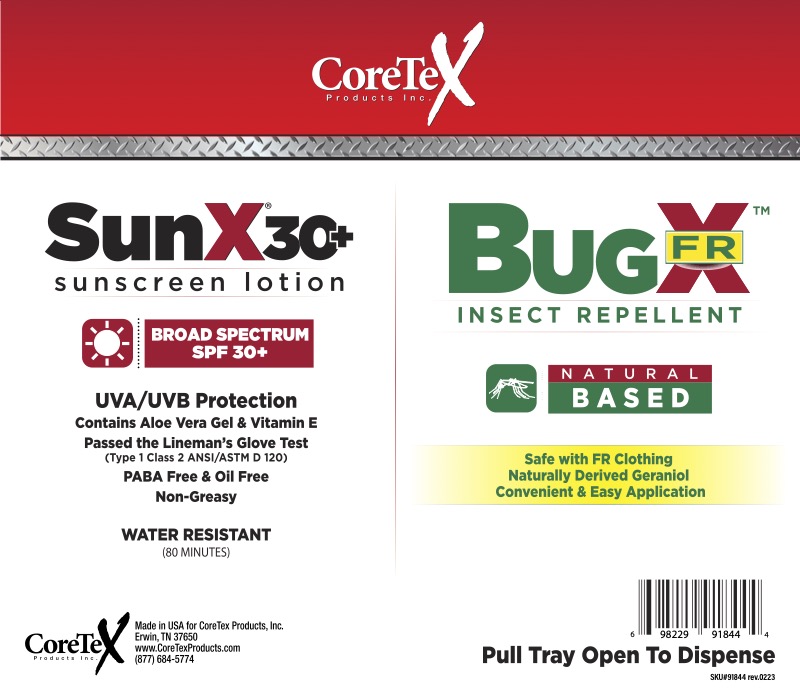 DRUG LABEL: SunX SPF 30/BugX Wallmount
NDC: 65753-511 | Form: KIT | Route: TOPICAL
Manufacturer: CoreTex Products Inc
Category: otc | Type: HUMAN OTC DRUG LABEL
Date: 20231022

ACTIVE INGREDIENTS: HOMOSALATE 5 g/100 mL; OCTINOXATE 7.5 g/100 mL; OCTISALATE 5 g/100 mL; AVOBENZONE 1 g/100 mL; OXYBENZONE 6 g/100 mL
INACTIVE INGREDIENTS: ACRYLATES/C10-30 ALKYL ACRYLATE CROSSPOLYMER (60000 MPA.S); ALKYL (C12-15) BENZOATE; ETHYLHEXYLGLYCERIN; ALOE VERA LEAF; PROPYLENE GLYCOL 1-CAPRYLATE; CARBOMER HOMOPOLYMER, UNSPECIFIED TYPE; EDETATE DISODIUM; PEG-6 SORBITAN OLEATE; THEOBROMA CACAO WHOLE; SODIUM HYDROXIDE; METHYLCELLULOSE, UNSPECIFIED; POLYSORBATE 20; PHENOXYETHANOL; MEDIUM DENSITY POLYETHYLENE; .ALPHA.-TOCOPHEROL ACETATE; WATER; PEG-100 STEARATE

SunX SPF 30/BugX Wallmount
65753-511

Active ingredients

Avobenzone 1.0%

Homosalate 5.0%

Octinoxate 7.5%

Octisalate 5.0%

Oxybenzone 6.0%

Purpose

Sunscreen

Sunscreen

Sunscreen

Sunscreen

Sunscreen

Uses

- helps prevent sunburn
- higher SPF gives more sunburn protetion.
- retains SPF after 80 minutes of activity in the water or sweating
- provides high protection against sunburn.

Warnings

For external use only.

Do not use

- on damaged or broken skin

When using this product

- keep out of the eyes. Rinse with water to remove.

Stop use and ask a doctor if

- rash or irritation develops and lasts

Keep out of the reach of children

If swallowed get medical help or contact a Poison Control center right away.

Directions

- apply liberally 15 minutes before sun exposure
- Reapply:
- after 80 minutes of swimming or sweating
- after towel drying, swimming , or
  - at least every 2 hours
- children under 6 months of age: Ask a doctor

Other information

- Protect this product from excessive heat or direct sun

Sun alert: Limiting sun exposure, wearing protective clothing, and using sunscreens may reduce the risk of skin aging, skin cancer, and other harmful effects of the sun.

Inactive ingredients

acrylates/C10-30 alkyl acrylate crosspolymer, aloe barbadensis leaf juice, C12-15 alkyl benzoate, carbomer, disodium EDTA, ethylexylglycerin, hydroxypropyl methylcellulose, phenoxyethanol, polyethylene, polysorbate 20, propylene glycol, sodium hydroxide, soritan oleate, theobroma cacao (cocoa) seed butter, tocopherol, tocopheryl acetate, water

Questions?

Call: 1-877-684-5774

SunX/BugX Kit Contents

50 count- SunX SPF 30, BugX 30